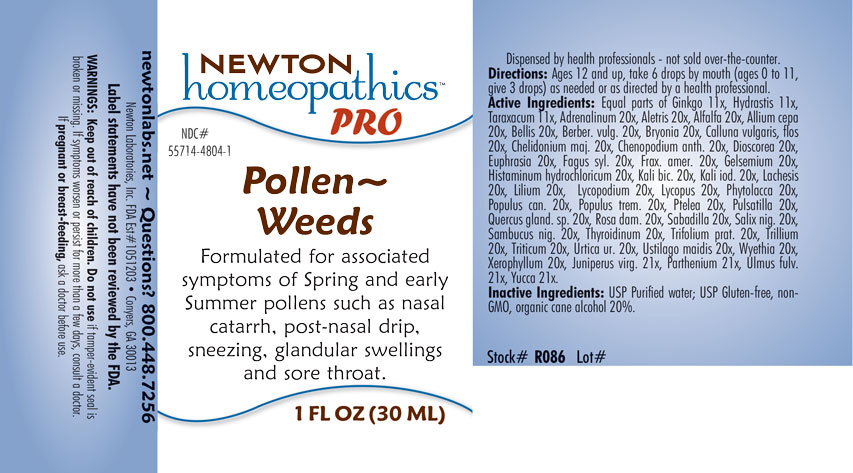 DRUG LABEL: Pollen-Weeds
NDC: 55714-4804 | Form: LIQUID
Manufacturer: Newton Laboratories, Inc.
Category: homeopathic | Type: HUMAN OTC DRUG LABEL
Date: 20201207

ACTIVE INGREDIENTS: CALLUNA VULGARIS FLOWERING TOP 20 [hp_X]/1 mL; ULMUS RUBRA BARK 21 [hp_X]/1 mL; FAGUS SYLVATICA NUT 20 [hp_X]/1 mL; FRAXINUS AMERICANA BARK 20 [hp_X]/1 mL; LILIUM LANCIFOLIUM WHOLE FLOWERING 20 [hp_X]/1 mL; BELLIS PERENNIS 20 [hp_X]/1 mL; ROSA DAMASCENA FLOWERING TOP 20 [hp_X]/1 mL; TRIFOLIUM PRATENSE FLOWER 20 [hp_X]/1 mL; SALIX NIGRA BARK 20 [hp_X]/1 mL; PARTHENIUM HYSTEROPHORUS 21 [hp_X]/1 mL; XEROPHYLLUM ASPHODELOIDES 20 [hp_X]/1 mL; EPINEPHRINE 20 [hp_X]/1 mL; ALFALFA 20 [hp_X]/1 mL; ALETRIS FARINOSA ROOT 20 [hp_X]/1 mL; ARTEMISIA VULGARIS ROOT 20 [hp_X]/1 mL; DYSPHANIA AMBROSIOIDES 20 [hp_X]/1 mL; LYCOPUS VIRGINICUS 20 [hp_X]/1 mL; PHYTOLACCA AMERICANA ROOT 20 [hp_X]/1 mL; POPULUS BALSAMIFERA LEAF BUD 20 [hp_X]/1 mL; POPULUS TREMULOIDES LEAF 20 [hp_X]/1 mL; PTELEA TRIFOLIATA BARK 20 [hp_X]/1 mL; SAMBUCUS NIGRA FLOWERING TOP 20 [hp_X]/1 mL; TRILLIUM ERECTUM ROOT 20 [hp_X]/1 mL; ELYMUS REPENS ROOT 20 [hp_X]/1 mL; URTICA URENS 20 [hp_X]/1 mL; WYETHIA HELENIOIDES ROOT 20 [hp_X]/1 mL; YUCCA FILAMENTOSA 21 [hp_X]/1 mL; USTILAGO MAYDIS 20 [hp_X]/1 mL; HISTAMINE DIHYDROCHLORIDE 20 [hp_X]/1 mL; JUNIPERUS VIRGINIANA TWIG 21 [hp_X]/1 mL; THYROID, UNSPECIFIED 20 [hp_X]/1 mL; ONION 20 [hp_X]/1 mL; ANTIMONY POTASSIUM TARTRATE 20 [hp_X]/1 mL; ARSENIC TRIOXIDE 20 [hp_X]/1 mL; BAPTISIA TINCTORIA ROOT 20 [hp_X]/1 mL; BERBERIS VULGARIS ROOT BARK 20 [hp_X]/1 mL; BRYONIA ALBA ROOT 20 [hp_X]/1 mL; CHELIDONIUM MAJUS 20 [hp_X]/1 mL; EUPHRASIA STRICTA 20 [hp_X]/1 mL; GELSEMIUM SEMPERVIRENS ROOT 20 [hp_X]/1 mL; POTASSIUM DICHROMATE 20 [hp_X]/1 mL; POTASSIUM IODIDE 20 [hp_X]/1 mL; LACHESIS MUTA VENOM 20 [hp_X]/1 mL; LYCOPODIUM CLAVATUM SPORE 20 [hp_X]/1 mL; ANEMONE PULSATILLA 20 [hp_X]/1 mL; SCHOENOCAULON OFFICINALE SEED 20 [hp_X]/1 mL; DIOSCOREA VILLOSA TUBER 20 [hp_X]/1 mL; GINKGO 11 [hp_X]/1 mL; TARAXACUM OFFICINALE 11 [hp_X]/1 mL; QUERCUS ROBUR NUT 20 [hp_X]/1 mL; GOLDENSEAL 11 [hp_X]/1 mL
INACTIVE INGREDIENTS: WATER; ALCOHOL

Pollen 4804L

INDICATIONS & USAGE SECTION

Formulated for associated symptoms of Spring and early Summer pollens such as nasal catarrh, post-nasal drip, sneezing, glandular swellings and sore throat,

DOSAGE & ADMINISTRATION SECTION

Directions: Ages 12 and up, take 6 drops by mouth (ages 0 to 11, give 3 drops) as needed or as directed by a health professional.

OTC - ACTIVE INGREDIENT SECTION

Equal parts of Ginkgo biloba 11x, Hydrastis canadensis 11x, Taraxacum officinale 11x, Adrenalinum 20x, Aletris farinosa 20x, Alfalfa 20x, Allium cepa 20x, Antimonium tartaricum 20x, Arsenicum album 20x, Artemisia vulgaris 20x, Baptisia tinctoria 20x, Bellis perennis 20x, Berberis vulgaris 20x, Bryonia 20x, Calluna vulgaris, flos 20x, Chelidonium majus 20x, Chenopodium anthelminticum 20x, Dioscorea vilosa 20x, Euphrasia officinalis 20x, Fagus sylvatica 20x, Fraxinus americana 20x, Gelsemium sempervirens 20x, Histaminum hydrochloricum 20x, Kali bichromicum 20x, Kali iodatum 20x, Lachesis mutus 20x, Lilium tigrinum 20x, Lycopodium clavatum 20x, Lycopus virginicus 20x, Phytolacca decandra 20x, Populus candicans 20x, Populus tremuloides 20x, Ptelea trifoliata 20x, Pulsatilla 20x, Quercus glandium spiritus 20x, Rosa damascena 20x, Sabadilla 20x, Salix nigra 20x, Sambucus nigra 20x, Thyroidinum 20x, Trifolium pratense 20x, Trillium pendulum 20x, Triticum repens 20x, Urtica urens 20x, Ustilago maidis 20x, Wyethia helenoides 20x, Xerophyllum asphodeloides 20x, Juniperus virginiana 21x, Parthenium 21x, Ulmus fulva 21x, Yucca filamentosa 21x.

INACTIVE INGREDIENT SECTION

Inactive Ingredients: USP Purified Water; USP Gluten-free, non-GMO, organic cane dispensing alcohol 20%.

QUESTIONS SECTION

newtonlabs.net – Questions? 800.448.7256

Newton Laboratories, Inc. FDA Est # 1051203 - Conyers, GA 30013

WARNINGS SECTION

Warnings: Keep out of reach of children. Do no use if tamper-evident seal is broken or missing. If symptoms worsen or persist for more than a few days, consult a doctor. If pregnant or breast-feeding, ask a doctor before use.

OTC - KEEP OUT OF REACH OF CHILDREN SECTION

Keep out of reach of children.